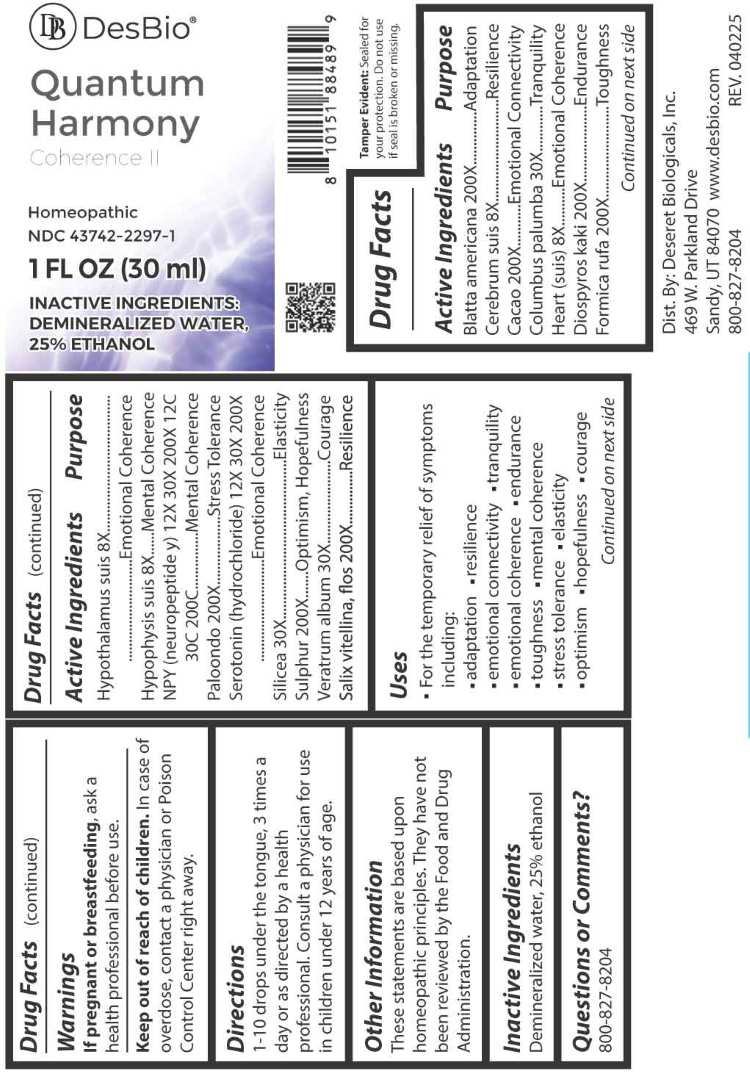 DRUG LABEL: Quantum Harmony
NDC: 43742-2297 | Form: LIQUID
Manufacturer: Deseret Biologicals, Inc.
Category: homeopathic | Type: HUMAN OTC DRUG LABEL
Date: 20260225

ACTIVE INGREDIENTS: PERIPLANETA AMERICANA 200 [hp_X]/1 mL; SUS SCROFA CEREBRUM 8 [hp_X]/1 mL; COCOA 200 [hp_X]/1 mL; HAIR KERATIN AMINO ACIDS 30 [hp_X]/1 mL; PORK HEART 8 [hp_X]/1 mL; PERSIMMON 200 [hp_X]/1 mL; FORMICA RUFA 200 [hp_X]/1 mL; SUS SCROFA HYPOTHALAMUS 8 [hp_X]/1 mL; SUS SCROFA PITUITARY GLAND 8 [hp_X]/1 mL; LARREA TRIDENTATA LEAF 200 [hp_X]/1 mL; NEUROPEPTIDE Y 12 [hp_X]/1 mL; SEROTONIN 12 [hp_X]/1 mL; SILICON DIOXIDE 30 [hp_X]/1 mL; SULFUR 200 [hp_X]/1 mL; VERATRUM ALBUM ROOT 30 [hp_X]/1 mL; SALIX ALBA FLOWERING TOP 200 [hp_X]/1 mL
INACTIVE INGREDIENTS: WATER; ALCOHOL

DRUG FACTS:

ACTIVE INGREDIENTS:

Blatta Americana 200X, Cerebrum Suis 8X, Cacao 200X, Columbus Palumba 30X , Heart (Suis) 8X, Diospyros Kaki 200X, Formica Rufa 200X, Hypothalamus Suis 8X, Hypophysis Suis 8X, Paloondo 200X, NPY (Neuropeptide Y) 12X, 30X, 200X, 12C, 30C, 200C, Serotonin (Hydrochloride) 12X, 30X, 200X, Silicea 30X, Sulphur 200X, Veratrum Album 30X, Salix Vitellina, Flos 200X.

PURPOSE:

Blatta Americana - Adaptation, Cerebrum Suis - Resilience, Cacao – Emotional Connectivity, Columbus Palumba - Tranquility, Heart (Suis) – Emotional Coherence, Diospyros Kaki - Endurance, Formica Rufa – Toughness, Hypothalamus Suis – Emotional Coherence, Hypophysis Suis – Mental Coherence, NPY (Neuropeptide Y) – Mental Coherence, Paloondo – Stress Tolerance, Serotonin (Hydrochloride) – Emotional Coherence, Silicea - Elasticity, Sulphur – Optimism, Hopefulness, Veratrum Album - Courage, Salix Vitellina, Flos - Resilience

USES:

• For the temporary relief of symptoms including:

• adaptation • resilience • emotional connectivity • tranquility • emotional coherence • endurance

• toughness • mental coherence • stress tolerance • elasticity • optimism • hopefulness • courage

These statements are based upon homeopathic principles. They have not been reviewed by the Food and Drug Administration.

WARNINGS:

If pregnant or breastfeeding, ask a health professional before use.

Keep out of reach of children. In case of overdose, contact a physician or Poison Control Center right away.

Tamper Evident: Sealed for your protection. Do not use if seal is broken or missing.

KEEP OUT OF REACH OF CHILDREN:

In case of overdose, contact a physician or Poison Control Center right away.

DIRECTIONS:

1-10 drops under the tongue, 3 times a day or as directed by a health professional. Consult a physician for use in children under 12 years of age.

INACTIVE INGREDIENTS:

Demineralized water, 25% ethanol

QUESTIONS:

Dist. By: Deseret Biologicals, Inc.

469 W. Parkland Drive

Sandy, UT 84070

www.desbio.com

800-827-8204

PACKAGE LABEL DISPLAY:

DesBio

Quantum Harmony

Coherence II

Homeopathic

NDC 43742-2297-1

1 FL OZ (30ml)